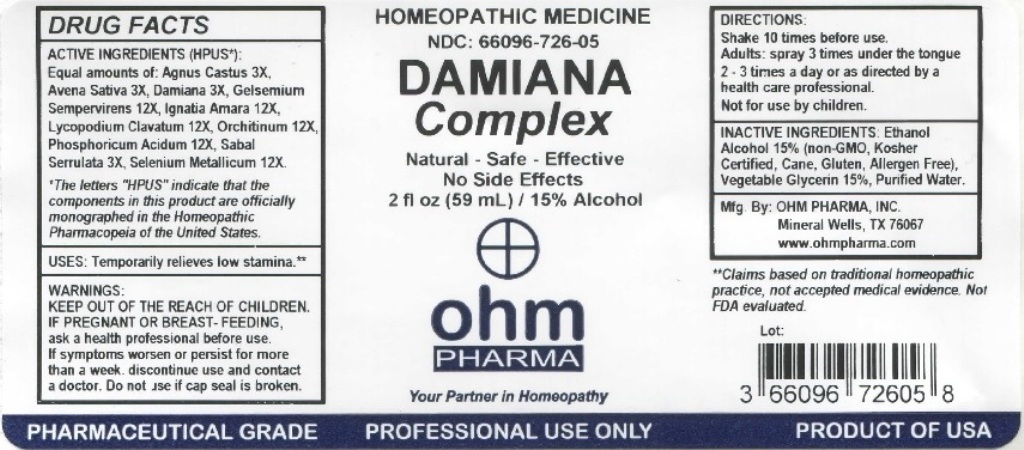 DRUG LABEL: Damiana Complex
NDC: 66096-726 | Form: LIQUID
Manufacturer: OHM PHARMA INC.
Category: homeopathic | Type: HUMAN OTC DRUG LABEL
Date: 20211229

ACTIVE INGREDIENTS: CHASTE TREE 3 [hp_X]/59 mL; AVENA SATIVA FLOWERING TOP 3 [hp_X]/59 mL; TURNERA DIFFUSA LEAFY TWIG 3 [hp_X]/59 mL; GELSEMIUM SEMPERVIRENS ROOT 12 [hp_X]/59 mL; STRYCHNOS IGNATII SEED 12 [hp_X]/59 mL; LYCOPODIUM CLAVATUM SPORE 12 [hp_X]/59 mL; SUS SCROFA TESTICLE 12 [hp_X]/59 mL; PHOSPHORIC ACID 12 [hp_X]/59 mL; SAW PALMETTO 3 [hp_X]/59 mL; SELENIUM 12 [hp_X]/59 mL
INACTIVE INGREDIENTS: ALCOHOL; GLYCERIN; WATER

OHM Damiana Complex

ACTIVE INGREDIENT

ACTIVE INGREDIENTS (HPUS*): Equal amounts of: Agnes Castus 3X, Avena Sativa 3X, Damiana 3X, Gelsemium Sempervirens 12X, Ignatia Amara 12X, Lycopodium Clavatum 12X, Orchitinum 12X, Phosphoricum Acidum 12X, Sabal Serrulata 3X, Selenium Metallicum 12X.

*The letters "HPUS" indicate that the components in this product are officially monographed in the Homeopathic Pharmacopeia of the United States.

INDICATIONS AND USAGE

USES: Temporarily relieves low stamina.**

** Claims based on traditional homepathic practice, not accepted medical evidence. Not FDA evaluated.

WARNINGS

WARNINGS: IF PREGNANT OR BREAST- FEEDING, ask a health professional before use. If symptoms worsen or persist for more than a week, discontinue use and contact a doctor.

- KEEP OUT OF REACH OF CHILDREN.

DOSAGE AND ADMINISTRATION

DIRECTIONS: Shake 10 times before use. Adults: spray 3 times under the tongue 2-3 times a day or as directed by a health care professional. Not for use by children.

Do not use if cap seal is broken.

INACTIVE INGREDIENT

INACTIVE INGREDIENTS: Ethanol Alcohol 15% (non-GMO, Kosher Certified, Cane, Gluten, Allergen Free), Vegetable Glycerin 15%, Purified Water.

QUESTIONS

Mfg. By: OHM PHARMA, INC. Mineral Wells, TX 76067

www.ohmpharma.com

PACKAGE LABEL

HOMEOPATHIC MEDICINE

NDC: 66096-726-05

DAMIANA Complex

Natural - Safe - Effective

No Side Effects

2 fl oz (59 mL) / 15% Alcohol

PRODUCT OF USA

PURPOSE

Temporarily relieves low stamina.